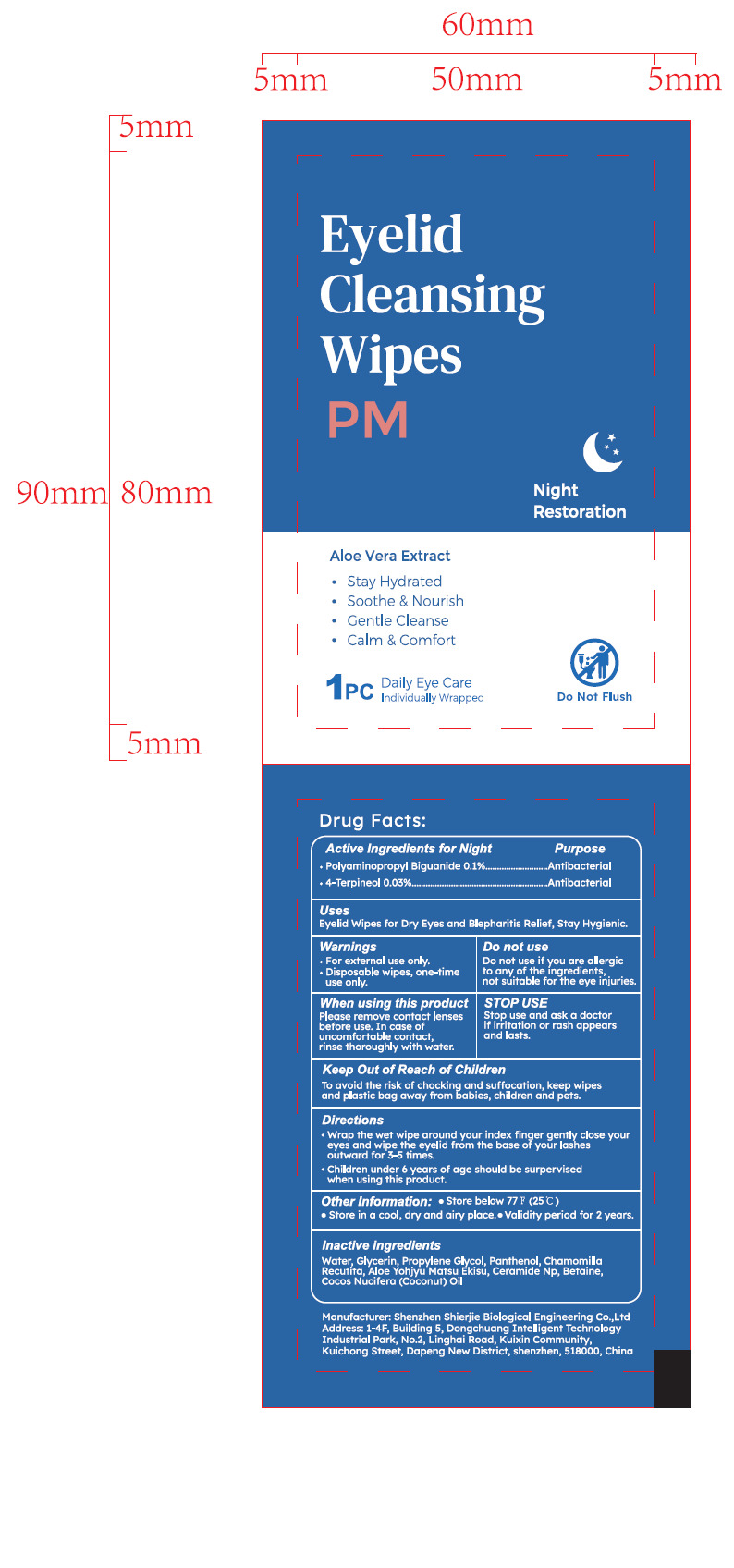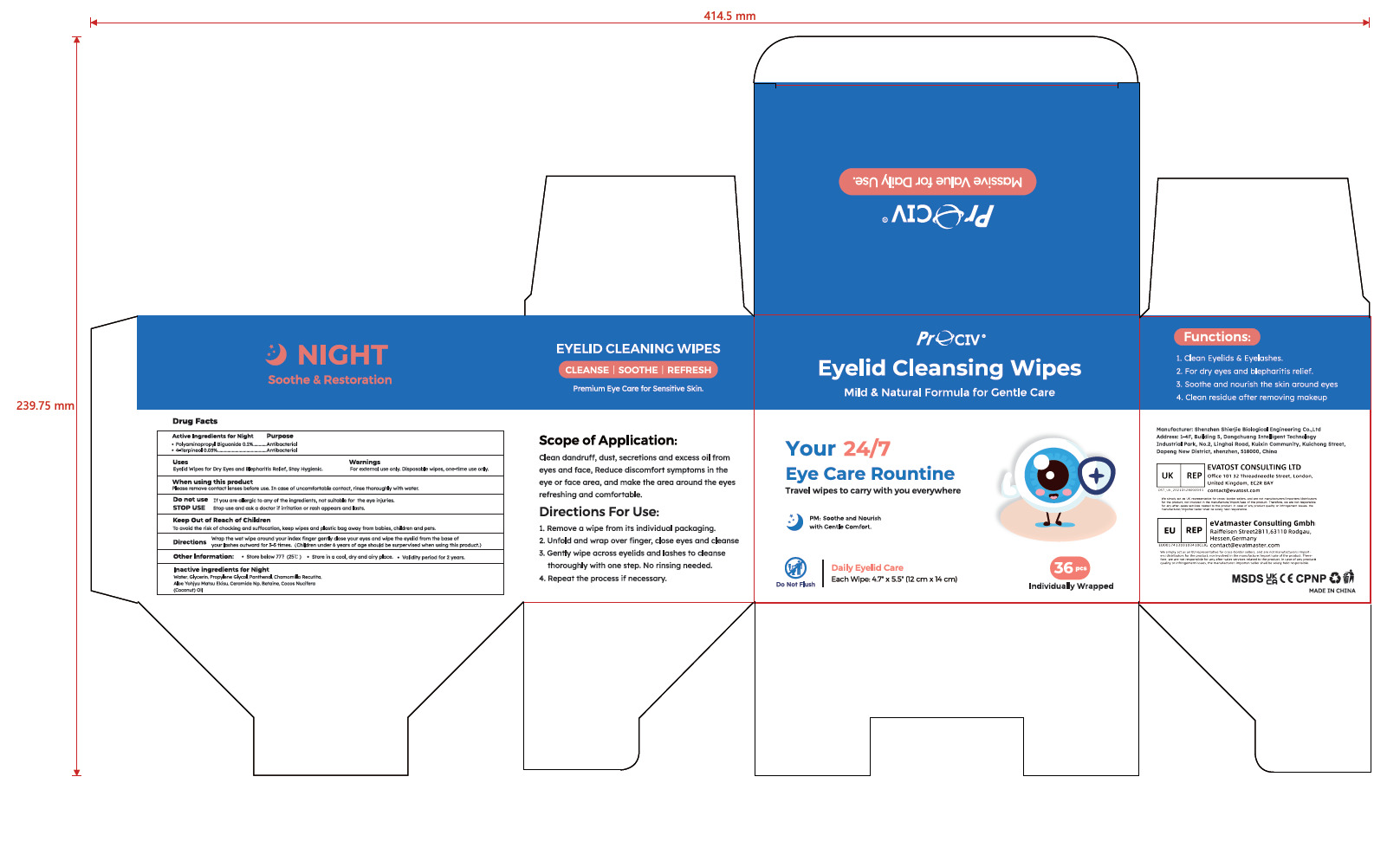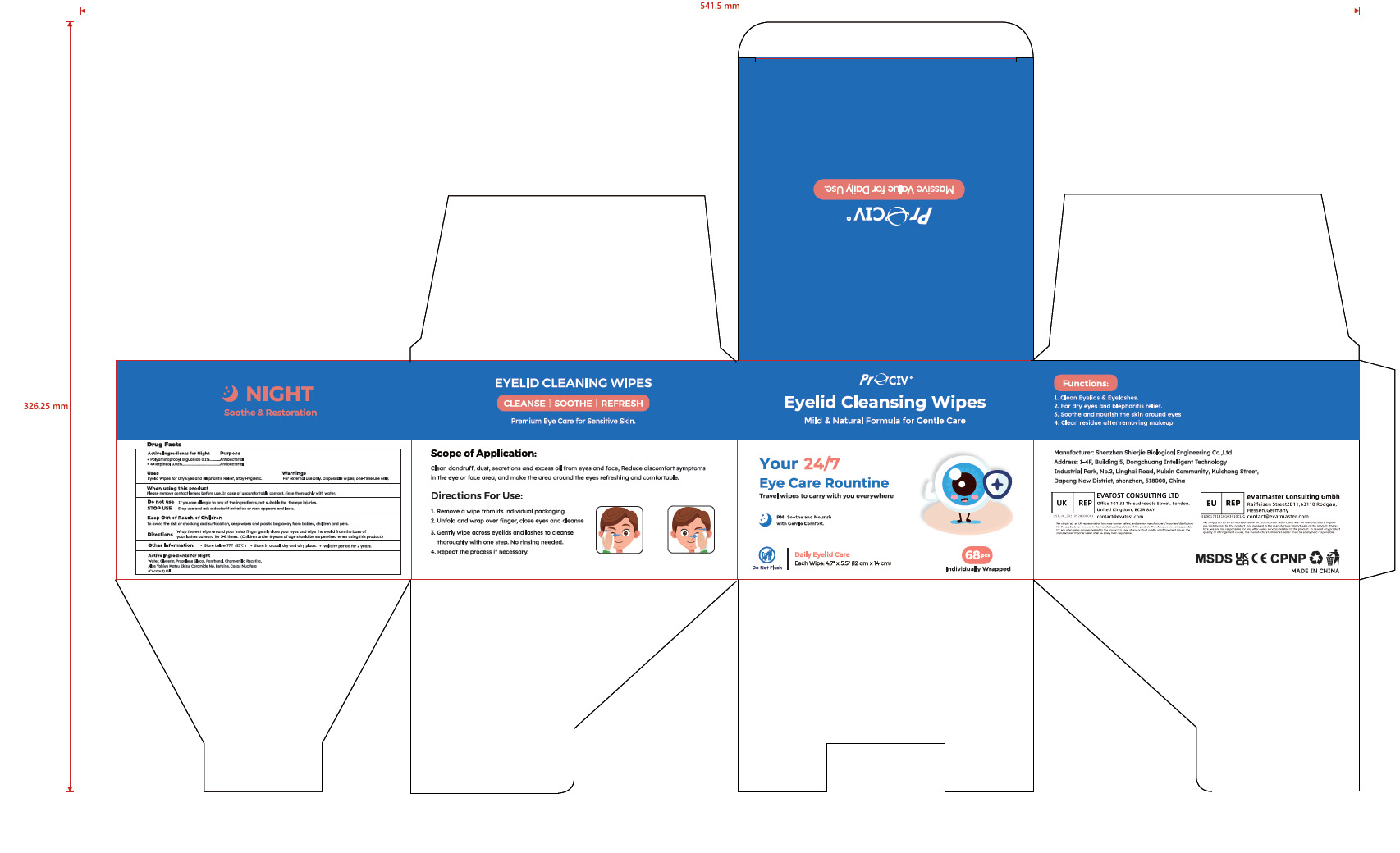 DRUG LABEL: Eyelid Cleansing Wipes
NDC: 43116-048 | Form: CLOTH
Manufacturer: Shenzhen Shierjie Biological Engineering Co., LTD
Category: otc | Type: HUMAN OTC DRUG LABEL
Date: 20251120

ACTIVE INGREDIENTS: POLYAMINOPROPYL BIGUANIDE 0.1 U/100 U; 4-TERPINEOL 0.03 U/100 U
INACTIVE INGREDIENTS: WATER; GLYCERIN; PROPYLENE GLYCOL; PANTHENOL; CHAMOMILE; ALOE VERA LEAF; CERAMIDE NP; BETAINE; COCOS NUCIFERA (COCONUT) OIL

43116-048

Active Ingredient

Polyaminopropyl Biguanide 0.1%

4-Terpineol 0.03%

Purpose

Antibacterial

Use

Eyelid Wipes for Dry Eyes and Blepharitis Relief, Stay Hygienic.

Warnings

●For external use only.
●Disposable wipes, one-time use only.

Do not use if you are allergic to any. of the ingredients, not suitable for the eye injuries.

When Using

Please remove contact lenses before use. In case of uncomfortable contact, rinse thoroughly with water.

Stop Use

Stop use and ask a doctor if irritation or rash appears and lasts.

Keep Oot Of Reach Of Children

To avoid the risk of chocking and suffocation, keep wipes and plastic bag away from babies, children and pets.

Directions

1.Wrap the wet wipe around your index finger gently close your eyes and wipe the eyelid from the base of your lashes
outward for 3-5 times.
2.Children under 6 years of age should be surpervised when using this product.

Other information

● Store below 77°F.(25"C)
● Store in a cool, dry and airy place.

● Validity period for 2 years.

Inactive ingredients

Water, Glycerin, Propylene Glycol, Panthenol, Chamomilla
Recutita, Aloe Yohjyu Matsu Ekisu, Ceramide Np, Betaine,
Cocos Nucifera (Coconut) Oil